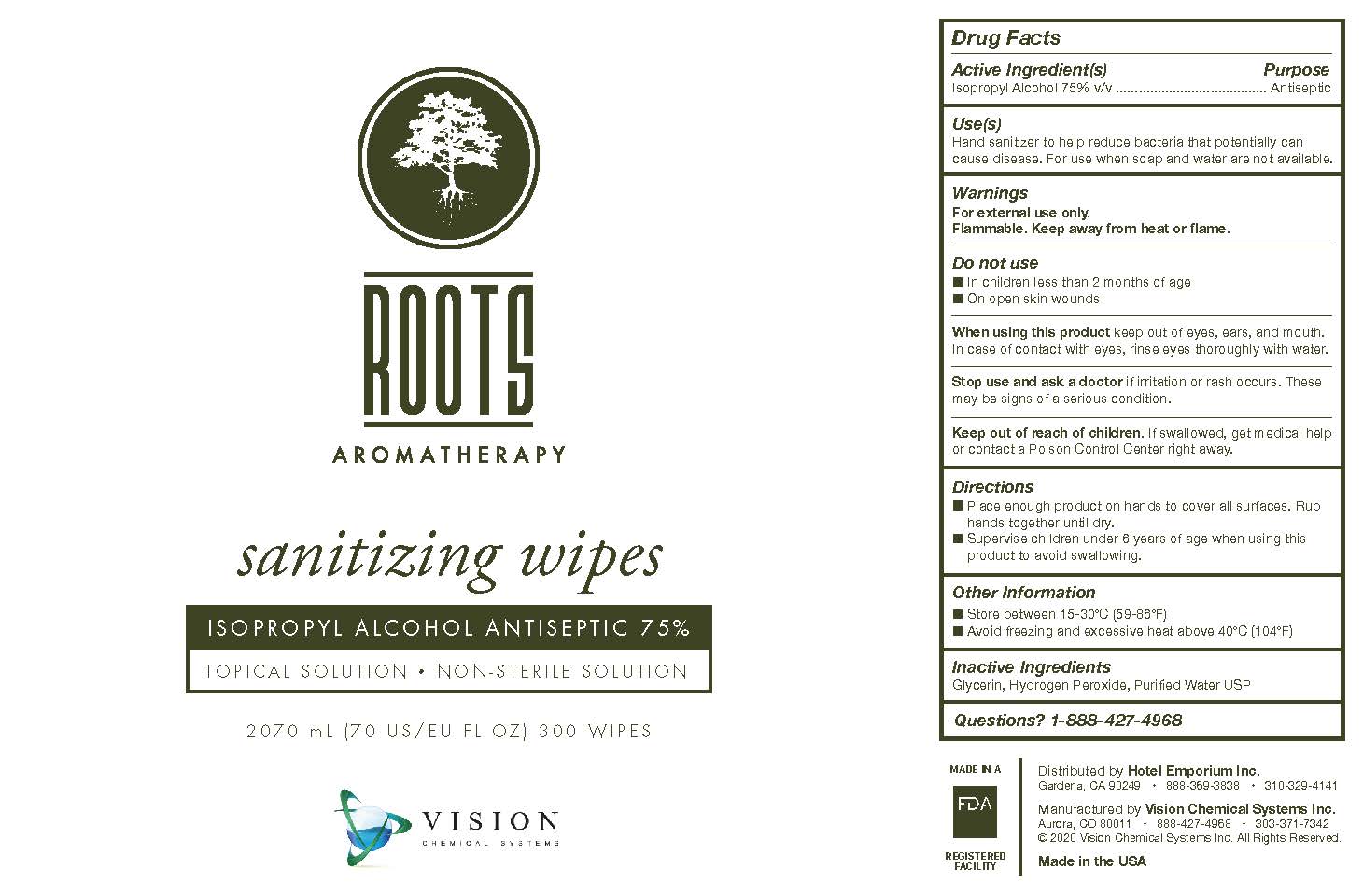 DRUG LABEL: Roots Aromatherapy
NDC: 76789-030 | Form: CLOTH
Manufacturer: Vision Chemical Systems
Category: otc | Type: HUMAN OTC DRUG LABEL
Date: 20220113

ACTIVE INGREDIENTS: ISOPROPYL ALCOHOL 75 mL/100 mL
INACTIVE INGREDIENTS: HYDROGEN PEROXIDE 0.125 mL/100 mL; WATER; GLYCERIN 1.45 mL/100 mL

Sanitizing Wipes

Active Ingredient(s)

Isopropyl Alcohol 75% v/v. Purpose: Antiseptic

Purpose

Antiseptic, Hand Sanitizer

Use

Hand Sanitizer to help reduce bacteria that potentially can cause disease. For use when soap and water are not available.

Warnings

For external use only. Flammable. Keep away from heat or flame.

Do Not Use

In children less than 2 months of age. On open skin wounds.

When using this product keep out of eyes, ears, and mouth. In case of contact with eyes, rinse eyes thoroughly with water.

Stop use and ask a doctor if irritation or rash occurs. These may be signs of a serious condition.

Keep out of reach of children. If swallowed, get medical help or contact a Poison Control Center right away.

Stop use and ask doctor if irritation or rash occurs. These may be signs of a serious condition.

Keep out of reach of children. If swallowed, get medical help or contact a Poison Control Center right away.

Directions

Rub wipes on hands or hard surfaces to sanitize.

Supervise children under 6 years of age when using this product to avoid swallowing.

Other Information

Store between 15-30C (59-86F)

Avoid freezing and excessive heat above 40C (104F)

Inactive Ingredients

Glycerin, Hydrogen Peroxide, Purified Water USP

PACKAGE LABEL

2070mL, 76789-030-01